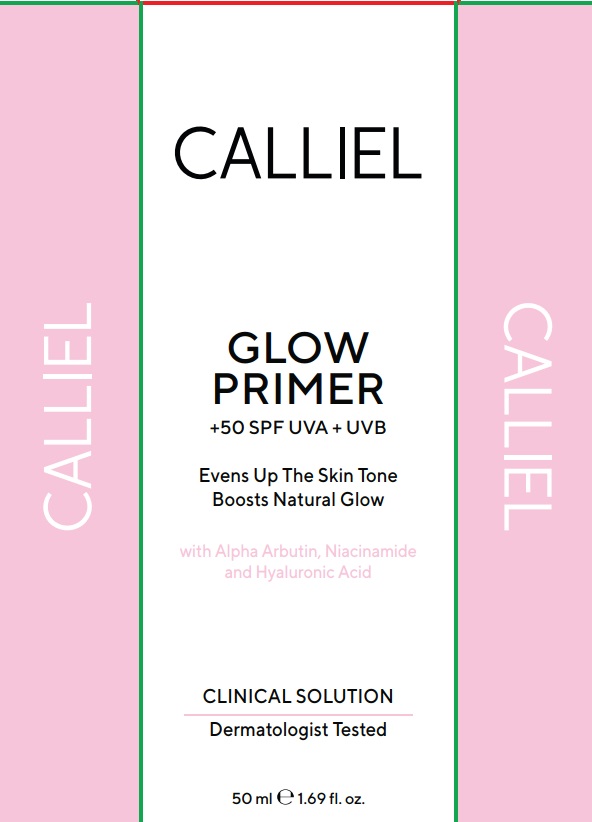 DRUG LABEL: CALLIEL GLOW PRIMER Broad Spectrum SPF 50 Sunscreen
NDC: 87411-0005 | Form: CREAM
Manufacturer: CALLIEL PHARMA KOZMETIK SANAYI VE TICARET ANONIM SIRKETI
Category: otc | Type: HUMAN OTC DRUG LABEL
Date: 20260207

ACTIVE INGREDIENTS: TITANIUM DIOXIDE 3 g/100 g; BUTYL METHOXYDIBENZOYLMETHANE 4.6 g/100 g; ETHYLHEXYL METHOXYCINNAMATE 8.5 g/100 g; OCTOCRYLENE 5 g/100 g; ZINC OXIDE 3.5 g/100 g
INACTIVE INGREDIENTS: GLYCERIN 1.6 g/100 g; CAPRYLYL GLYCOL 0.12 g/100 g; ANHYDROXYLITOL 0.32 g/100 g; PHENOXYETHANOL 0.82 g/100 g; ARACHIDYL ALCOHOL 0.32 g/100 g; GLYCERYL STEARATE 3.2 g/100 g; CETEARETH-20 3.2 g/100 g; CAPRYLIC/CAPRIC TRIGLYCERIDE 1.63 g/100 g; CI 77491 0.12 g/100 g; C12-15 ALKYL BENZOATE 5.6 g/100 g; ARACHIDYL GLUCOSIDE 0.18 g/100 g; ALOE BARBADENSIS LEAF JUICE 0.12 g/100 g; TRIETHOXYCAPRYLYLSILANE 0.01 g/100 g; CETEARYL ALCOHOL 5.2 g/100 g; XYLITYLGLUCOSIDE 1.3 g/100 g; DIMETHICONE 1.61 g/100 g; ALPHA-ARBUTIN 1.52 g/100 g; NIACINAMIDE 3.2 g/100 g; BUTYROSPERMUM PARKII (SHEA) BUTTER 2.5 g/100 g; XYLITOL 0.32 g/100 g; XANTHAN GUM 0.16 g/100 g; BEHENYL ALCOHOL 0.32 g/100 g; AQUA 41.51 g/100 g; HYALURONIC ACID 0.12 g/100 g

Active Ingredients

Ethylhexyl Methoxycinnamate 8.51%

Octocrylene 5%

Butyl Methoxydibenzoylmethane 4.6%

Zinc Oxide 3.5%

Titanium Dioxide 3%

Uses

• helps prevent sunburn
• if used as directed with other sun protection measures (see Directions), decreases the risk of skin cancer and early skin aging caused by the sun

Do not use on damaged or broken skin

Stop use and ask a doctor if rash occurs.

Keep out of reach of children. If swallowed, get medical help or contact a Poison Control Center right away.

Directions

• apply liberally 15 minutes before sun exposure
• reapply:
• after 80 minutes of swimming or sweating
• immediately after towel drying
• at least every 2 hours
• children under 6 months: Ask a doctor

Sun Protection Measures: Spending time in the sun increases your risk of skin cancer and early skin aging caused by the sun. To decrease this risk, regularly use a sunscreen with a Broad Spectrum SPF 15 or higher and other sun protection measures including:
• limit time in the sun, especially from 10 a.m. – 2 p.m.
• wear long-sleeve shirts, pants, hats, and sunglasses

Warnings

For external use only

Purpose

Sunscreen

Inactive ingredients

Aqua, C12-15 Alkyl Benzoate, Cetearyl Alcohol, Glyceryl Stearate, Ceteareth-20, Niacinamide, Butyrospermum Parkii Butter, Caprylic/Capric Triglyceride, Dimethicone, Glycerin, Alpha-Arbutin, Xylitylglucoside, Phenoxyethanol, Arachidyl Alcohol, Anhydroxylitol, Behenyl Alcohol, Xylitol, Arachidyl Glucoside, Xanthan Gum, Aloe Barbadensis Leaf Extract, CI 77491, Hyaluronic Acid, Caprylyl Glycol, Triethoxycaprylylsilane.

PACKAGE LABEL

CALLIEL

GLOW PRIMER

Broad Spectrum SPF 50 Sunscreen

Helps Protect Skin from Sunburn
Enhances Natural Radiance

with Alpha Arbutin, Niacinamide
and Hyaluronic Acid

Dermatologist Tested

50 mL (1.69 fl oz)